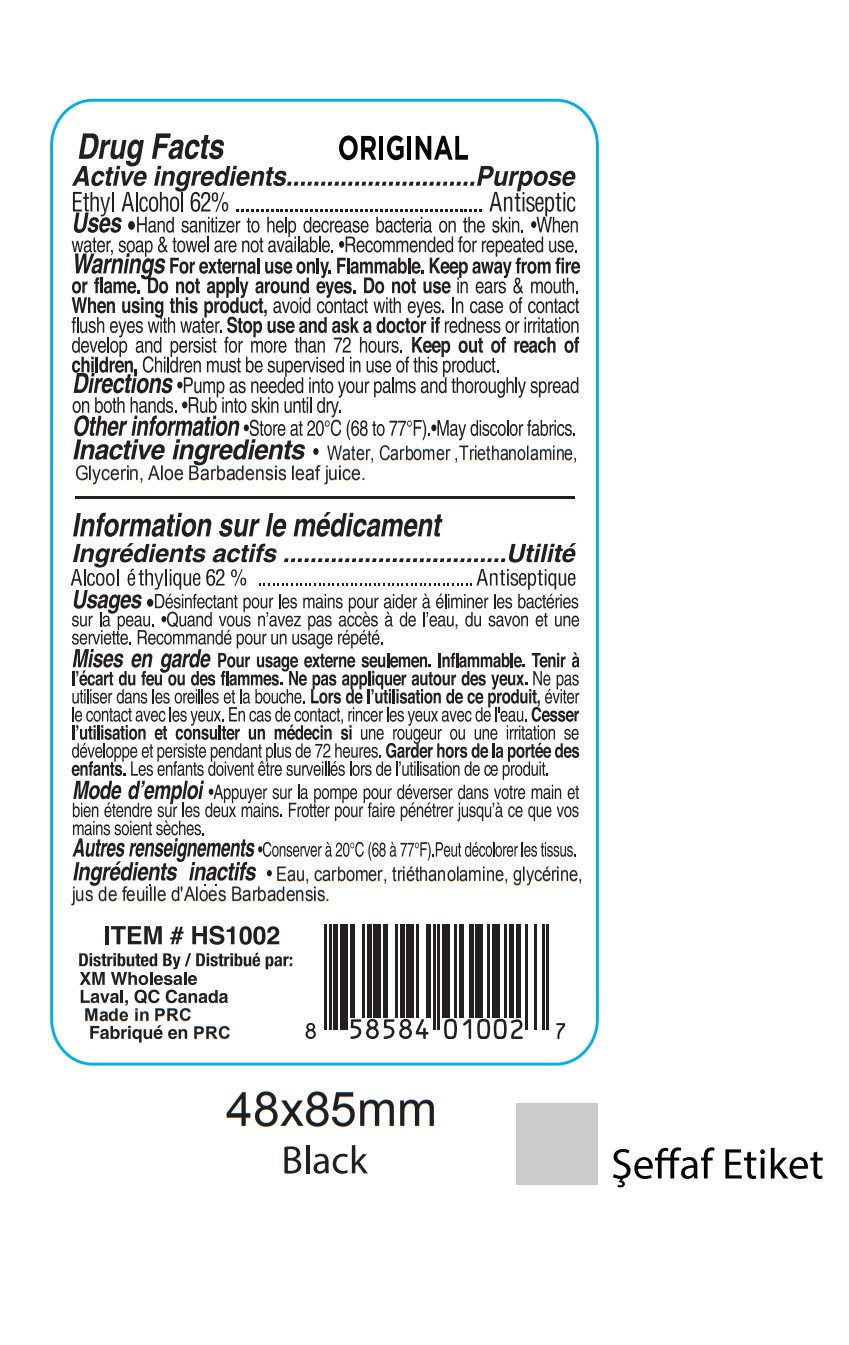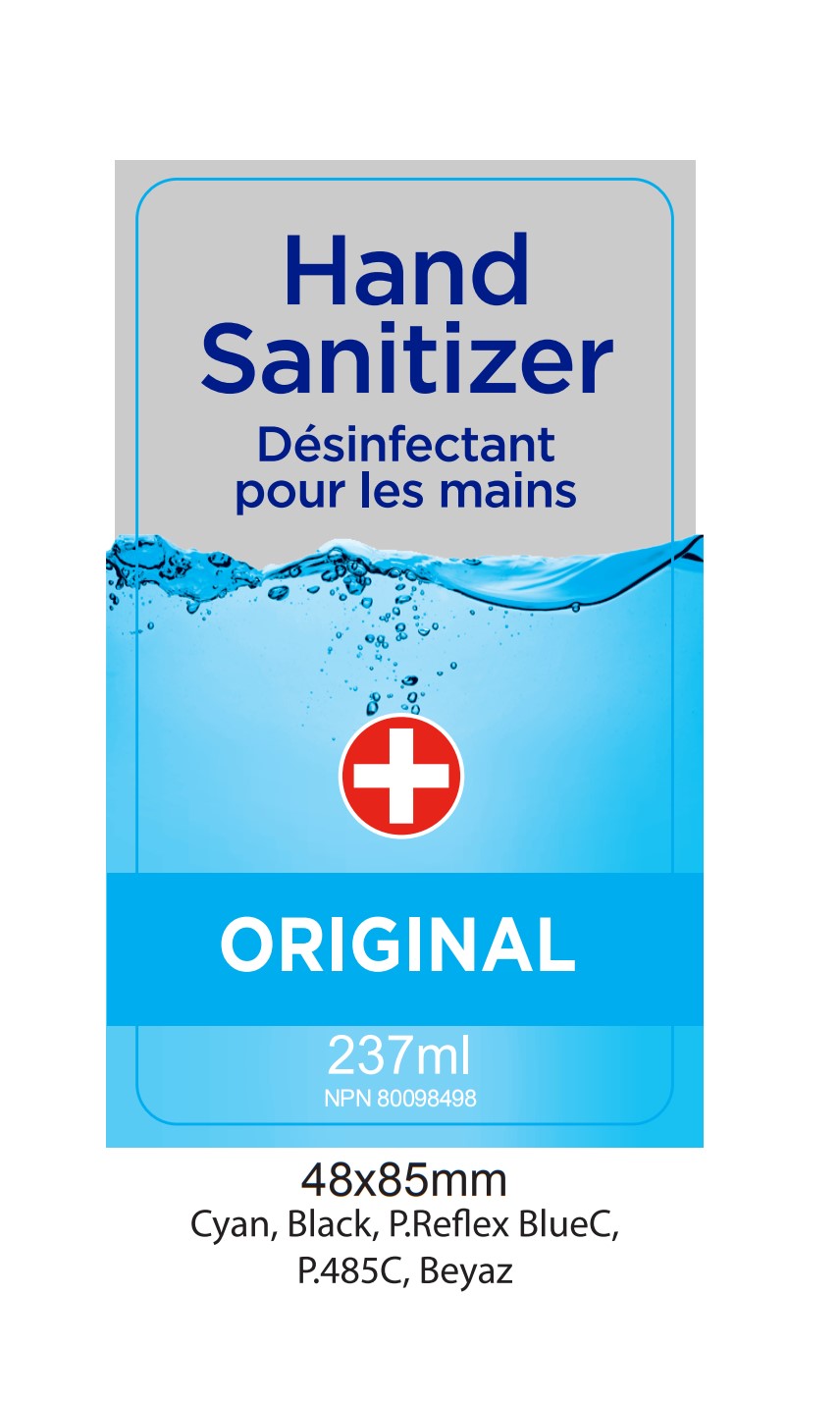 DRUG LABEL: Hand Sanitizer Original
NDC: 76114-004 | Form: SOLUTION
Manufacturer: Zhejiang Aidi Cosmetics Co., Ltd
Category: otc | Type: HUMAN OTC DRUG LABEL
Date: 20200424

ACTIVE INGREDIENTS: ALCOHOL 62 mL/100 mL
INACTIVE INGREDIENTS: GLYCERIN; WATER; CARBOMER 934; TRIETHANOLAMINE SULFATE; ALOE VERA WHOLE

NA

Active Ingredient(s)

Ethyl Alcohol 62% v/v

Purpose

Antiseptic

Use

Hand sanitizer to help reduce bacteria on the skin

When water, soap, and towel are not available

Recommended for repeaded use

Warnings

For external use only.

Flammable. Keep away from fire or flame

WHEN USING

Do not apply around eyes

Do not use in ears and mouth

When using this product avoid contact with eyes. In case of contact, flush eyes with water.

Stop use and ask a doctor if redness or irritation develops and persists for more than 72 hours

Keep out of reach of children. Children must be supervised in use of this product.

Directions

Pump as needed into your palms and thoroughly spread on both hands. Rub into skin until dry.

Other information

Store at 20C (68-77F)

May discolor fabrics

Inactive ingredients

Water, carbomer, triethanolamine, glycerin, aloe barbadensis leaf jiuce